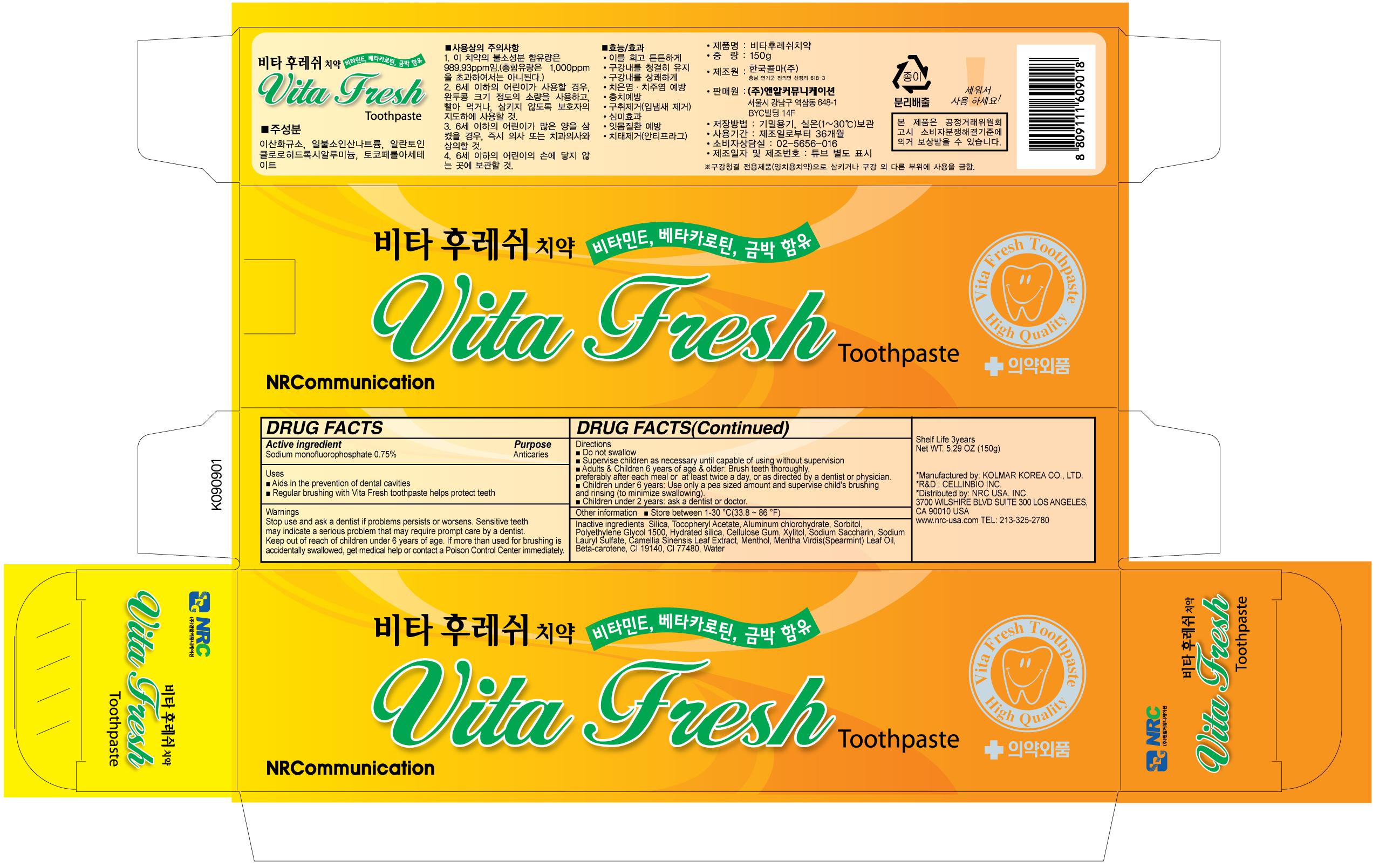 DRUG LABEL: Vita Fresh
NDC: 76173-1003 | Form: PASTE, DENTIFRICE
Manufacturer: Cellinbio Co Ltd
Category: otc | Type: HUMAN OTC DRUG LABEL
Date: 20110727

ACTIVE INGREDIENTS: SODIUM MONOFLUOROPHOSPHATE 1.125 g/150 g
INACTIVE INGREDIENTS: SILICON DIOXIDE; ALPHA-TOCOPHEROL ACETATE; ALUMINUM CHLOROHYDRATE; SORBITOL; POLYETHYLENE GLYCOL 1500; HYDRATED SILICA; CARBOXYMETHYLCELLULOSE SODIUM; XYLITOL; SACCHARIN SODIUM; SODIUM LAURYL SULFATE; GREEN TEA LEAF; LEVOMENTHOL; SPEARMINT OIL; BETA CAROTENE; FD&C YELLOW NO. 5; GOLD; WATER

Vita Fresh Toothpaste

Drug Facts

Active ingredient
Sodium monofluorophosphate 0.75%

Purpose

Anticaries

Keep out of reach of children under 6 years of age. If more than used for brushing is accidentally swallowed, get medical help or contact a Poison Control Center immediately.

Indication & Usage

Directions
Do not swallow
Supervise children as necessary until capable of using without supervision
Adults, Children 6 years of age, older: Brush teeth thoroughly, preferably after each meal or at least twice a day, or as directed by a dentist or physician.
Children under 6 years: Use only a pea sized amount and supervise child's brushing and rinsing(to minimize swallowing).
Children under 2 years: ask a dentist or doctor.

Warnings

Stop use and ask a dentist if problems persists or worsens. Sensitive teeth may indicate a serious problem that may require prompt care by a dentist.

Dosage & Administration

Enter section text here

Inactive Ingredient

Silica, Tocopheryl Acetate, Aluminum chlorohydrate, Sorbitol, Polyethylene Glycol 1500, Hydrated silica, Cellulose Gum, Xylitol, Sodium Saccharin, Sodium Lauryl Sulfate, Camellia Sinensis Leaf Extract, Menthol, Mentha Virdis(Spearmint) Leaf Oil, Beta-carotene, CI 19140, CI 77480, Water

Vita Fresh Toothpaste

NRC Vita Fresh Toothpaste

Net WT. 5.29 OZ(150g)